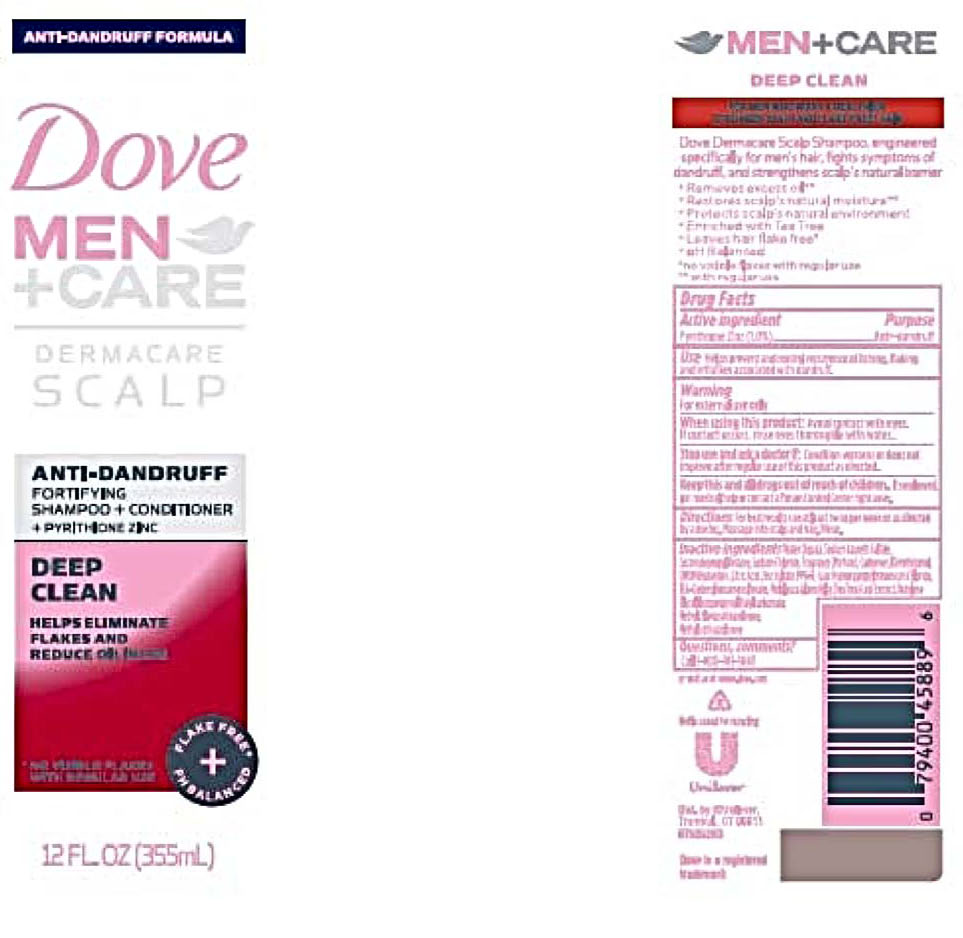 DRUG LABEL: Dove
NDC: 64942-1621 | Form: LIQUID
Manufacturer: Conopco, Inc. d/b/a/ Unilever
Category: otc | Type: HUMAN OTC DRUG LABEL
Date: 20221207

ACTIVE INGREDIENTS: PYRITHIONE ZINC 1 g/100 mL
INACTIVE INGREDIENTS: LAURETH-23; ALMOND OIL; WATER; SODIUM LAURETH-3 SULFATE; COCAMIDOPROPYL BETAINE; SODIUM CHLORIDE; DIMETHICONOL (40 CST); CARBOMER HOMOPOLYMER TYPE C; DIMETHICONE; DMDM HYDANTOIN; GUAR HYDROXYPROPYLTRIMONIUM CHLORIDE (1.7 SUBSTITUENTS PER SACCHARIDE); CITRIC ACID MONOHYDRATE; ZINC SULFATE, UNSPECIFIED FORM; TRIETHANOLAMINE DODECYLBENZENESULFONATE; BUTYLENE GLYCOL; .ALPHA.-TOCOPHEROL ACETATE, D-; PANTHENOL; PPG-9; IODOPROPYNYL BUTYLCARBAMATE; METHYLCHLOROISOTHIAZOLINONE; METHYLISOTHIAZOLINONE; POLOXAMER 407; LAURETH-4; POLYETHYLENE GLYCOL 200; TEA TREE OIL; SOYBEAN OIL; COCONUT OIL; SPEARMINT OIL; ASIAN GINSENG; MENTHOL; LYSINE HYDROCHLORIDE; XANTHAN GUM; SUNFLOWER OIL

Dove Men+Care Dermacare Scalp Deep Clean Anti-Dandruff Shampoo + Conditioner

DOVE MEN+CARE DERMACARE SCALP DEEP CLEAN ANTI-DANDRUFF SHAMPOO + CONDITIONER - pyrithione zinc liquid

Dove Men+Care Dermacare Scalp Deep Clean Anti-Dandruff Shampoo + Conditioner

Drug Facts

Active ingredient
Pyrithione Zinc (1.0%)

Purpose

Anti-dandruff

Use

• Helps prevent and control recurrence of itching. flaking and irritation associated with dandruff.

Warnings

• For external use only
• When using this product: Avoid contact with eyes. If contact occurs, rinse eyes thoroughtly with water.
• Stop use and ask a doctor if: Condition worsens or does not improve after regular use of this product as directed.

KEEP OUT OF REACH OF CHILDREN

• Keep this and all drugs out of reach of children.
If swallowed, get medical help or contact a Poison Control Center right away.

Directions

For best results use at least twice per week or as directed by a doctor. Massage into scalp and hair. Rinse.

Inactive Ingredients

Water (Aqua), Sodium Laureth Sulfate, Cocamidopropyl Betaine, Sodium Chloride, Fragrance (Parfum), Carbomer, Dimethiconol, DMDM Hydantoin, Citric Acid, Zinc Sulfate, PPG-9, Guar Hydroxypropyltrimonium Chloride, TEA-Dodecylbenzenesulfonate, Melaleuca Alternifolia (Tea Tree) Leaf Extract, Butylene Glycol, Iodopropynyl Butylcarbamate, Methylchloroisothiazolinone, Methylisothiazolinone.

Questions, comments?

Call 1-800-761-3683